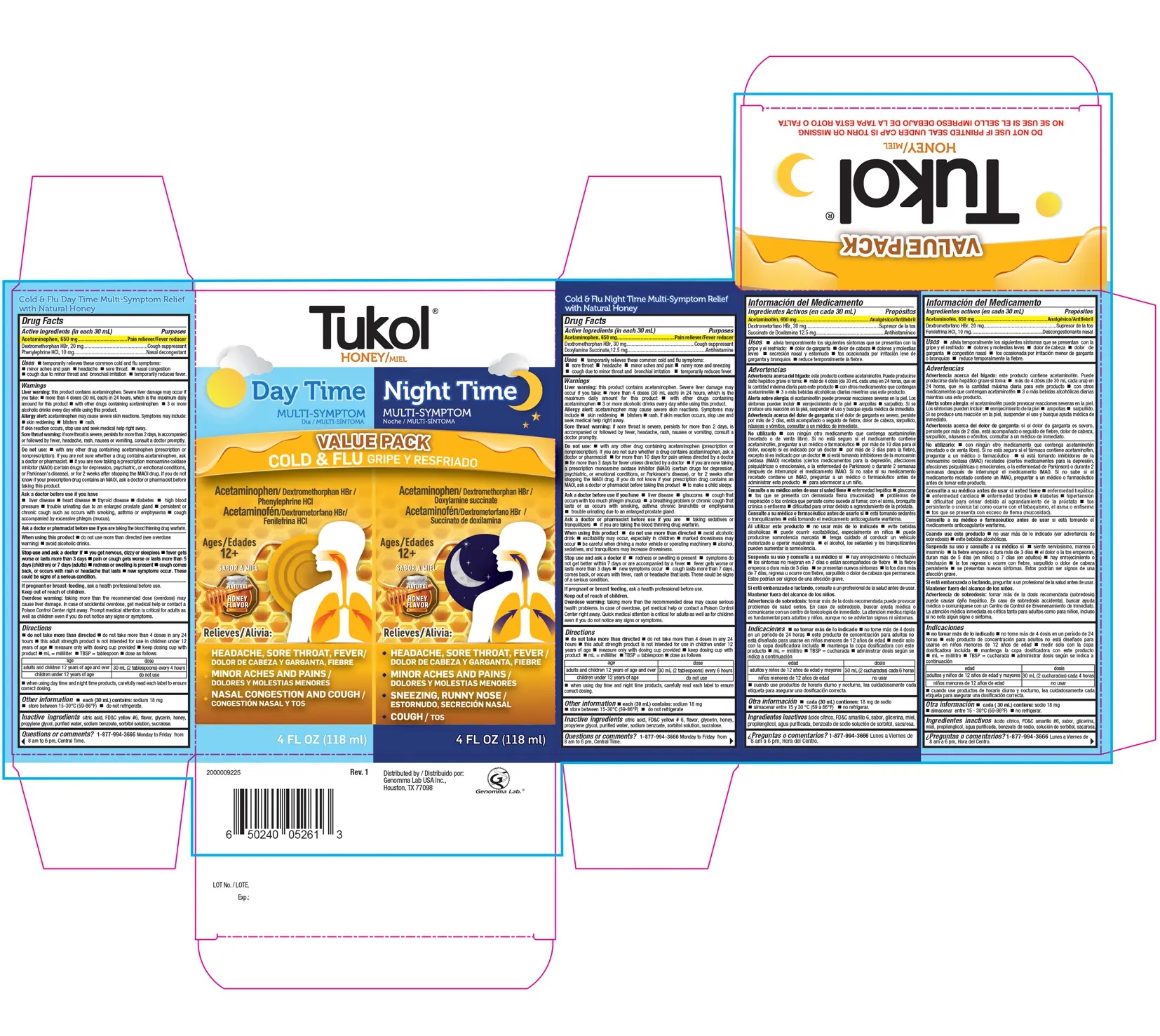 DRUG LABEL: Tukol Honey Daytime and Nighttime Value Pack
NDC: 50066-304 | Form: KIT | Route: ORAL
Manufacturer: Genomma Lab USA
Category: otc | Type: HUMAN OTC DRUG LABEL
Date: 20241022

ACTIVE INGREDIENTS: ACETAMINOPHEN 21.667 mg/1 mL; DEXTROMETHORPHAN HYDROBROMIDE 0.667 mg/1 mL; PHENYLEPHRINE HYDROCHLORIDE 0.333 mg/1 mL; ACETAMINOPHEN 21.667 mg/1 mL; DEXTROMETHORPHAN HYDROBROMIDE 1 mg/1 mL; DOXYLAMINE SUCCINATE 0.4167 mg/1 mL
INACTIVE INGREDIENTS: ANHYDROUS CITRIC ACID; FD&C YELLOW NO. 6; HONEY; WATER; GLYCERIN; PROPYLENE GLYCOL; SORBITOL; SODIUM BENZOATE; SUCRALOSE; ANHYDROUS CITRIC ACID; FD&C YELLOW NO. 6; HONEY; WATER; GLYCERIN; PROPYLENE GLYCOL; SORBITOL; SODIUM BENZOATE; SUCRALOSE

Tukol®Honey Daytime & Nighttime Value Pack

Cold & Flu Day Time Multi-Symptom Relief with Natural Honey

Drug Facts

ACTIVE INGREDIENT

Active Ingredients (in each 30 mL) | Purpose
Acetaminophen 650 mg | Pain reliever/Fever reducer
Dextromethorphan HBr 20 mg | Cough suppressant
Phenylephrine HCl 10 mg | Nasal Decongestant

Uses

Temporarily relieves these common cold and flu symptoms

- minor aches and pain
- headache
- sore throat
- nasal congestion
- cough due to minor throat and bronchial irritation
- temporarily reduces fever

Warnings

Liver warning

The product contains Acetaminophen. Severe liver damage may occur if you take

- more than 4 doses (30 mL each) in 24 hours, which is the maximum daily amount for this product
- with other drugs containing acetaminophen
- 3 or more alcoholic drinks every day while using this product.

Allergy alert

Acetaminophen may cause severe skin reactions. Symptoms may include

- skin reddening
- blisters
- rash.

If skin reaction occurs, stop use and seek medical help right away.

Sore throat warning

If sore throat is severe, persists for more than 2 days, is accompanied or followed by fever, headache, rash, nausea or vomiting, consult a doctor promptly.

Do not use

- with any other drug containing acetaminophen (prescription or nonprescription). If you are not sure whether a drug contains acetaminophen, ask a doctor or pharmacist.
- if you are now taking a prescription monoamine oxidase inhibitor (MAOI) (certain drugs for depression, psychiatric, or emotional conditions, or Parkinson's disease), or for two weeks after stopping the MAOI drug. If you do not know if your prescription drug contains an MAOI, ask a doctor or pharmacist before taking this product.

Ask a doctor before use if you have

- liver disease
- heart disease
- thyroid disease
- diabetes
- high blood pressure
- trouble urinating due to an enlarged prostate gland
- persistent or chronic cough such as occurs with smoking, asthma or emphysema
- cough accompanied by excessive phlegm (mucus)

Ask a doctor or pharmacist before use

- if you are taking the blood thinning drug warfarin

When using this product

- do not use more than directed (see overdose warning)
- avoid alcoholic drinks

Stop use and ask a doctor if

- you get nervous, dizzy or sleepless
- fever gets worse or lasts more than 3 days
- pain or cough gets worse or lasts more than 5 days (children) or 7 days (adults)
- redness or swelling is present
- cough comes back, or occurs with rash or headache that lasts.
- new symptoms occur
- These could be signs of a serious condition.

PREGNANCY OR BREAST FEEDING

If pregnant or breast feeding,ask a health professional before use.

Keep out of reach of children.

Overdose warning

Taking more than the recommended dose (overdose) may cause liver damage. In case of overdose, get medical help or contact a Poison Control Center right away. Prompt medical attention is critical for adults as well as for children even if you do not noticve any signs or symptoms.

Directions

- do not take more than directed
- do not take more than 4 doses in any 24 hours
- this adult strength product is not intended for use in children under 12 years of age
- measure only with dosing cup provided
- keep dosing cup with product
- mL = mililiter
- TBSP = tablespoon
- dose as follows

Adults and children 12 years or age and over | 30 mL (2 tablespoons) every 4 hours
Children under 12 years | Do not use
- When using Day Time and Night Time products, carefully read each label to ensure correct dosing.

Other information

- Each 30 mL contains sodium: 18 mg
- store between 15-30oC (59-86oF)
- do not refrigerate

Inactive ingredients

Citric acid, FD&C Yellow # 6, flavor, glycerin, honey, propylene glycol, purified water, sodium benzoate, sorbitol solution, sucralose

Questions or comments?

1-877-994-3666

Monday to Friday from 8 am to 6 pm, Central Time

Cold & Flu Night Time Multi-Symptom Relief with Natural Honey

Drug Facts

ACTIVE INGREDIENT

Active Ingredients (in each 30 mL) | Purpose
Acetaminophen 650 mg | Pain reliever/Fever reducer
Dextromethorphan HBr 30 mg | Cough suppressant
Doxylamine Succinate 12.5 mg | Antihistamine

Uses

Temporarily relieves these common cold and flu symptoms:

- sore throat
- headache
- minor aches and pain
- runny nose and sneezing
- cough due to minor throat and bronchial irritation
- temporarily reduces rever

Warnings

Liver warning

The product contains Acetaminophen. Severe liver damage may occur if you take

- more than 4 doses (30 mL each) in 24 hours, which is the maximum daily amount for this product
- with other drugs containing acetaminophen
- 3 or more alcoholic drinks every day while using this product.

Allergy alert

Acetaminophen may cause severe skin reactions. Symptoms may include

- skin reddening
- blisters
- rash.

If skin reaction occurs, stop use and seek medical help right away.

Sore throat warning

If sore throat is severe, persists for more than 2 days, is accompanied or followed by fever, headache, rash, nausea or vomiting, consult a doctor promptly.

Do not use

- with any other drug containing acetaminophen (prescription or nonprescription). if you are not sure whether a drug contains acetaminophen, ask a doctor or pharmacist
- for more than 10 days for pain unless directed by a doctor.
- for more than 3 days for fever unless directed by a doctor
- if you are now taking a prescription monoamine oxidase inhibitor (MAOI) (certain drugs for depression, psychiatric, or emotional conditions, or Parkinson's disease), or for 2 weeks after stopping the MAOI drug. If you do not know if your prescription drug contains an MAOI, ask a doctor or pharmacist before taking this product.
- to make a child sleepy

Ask a doctor before use if you have

- liver disease
- glaucoma;
- cough that occurs with too much phlegm (mucus)
- a breathing problem or chronic cough that lasts or as occurs with smoking, asthma, chronic bronchitis or emphysema
- trouble urinating due to an enlarged prostate gland.

Ask a doctor or pharmacist before use

- if you are taking sedatives or tranquillizers
- if you are taking the blood thinning drug warfarin

When using this product

- do not use more than directed
- avoid alcoholic drinks
- excitability may occur, especially in children,
- marked drowsiness may occur
- be careful when driving a motor vehicle or operating machinery
- alcohol, sedatives, and tranquilizers may increase drowsiness

Stop use and ask a doctor if

- redness or swelling is present
- symptoms do not get better within 7 days or are accompanied by a fever
- fever gets worse or lasts more than 3 days
- new symptoms occur
- cough lasts more than 7 days, comes back, or occurs with fever, rash or headache that lasts. These could be signs of a serious condition.

PREGNANCY OR BREAST FEEDING

If pregnant or breast feeding,ask a health professional before use.

Keep out of reach of children.

Overdose warning

Taking more than the recommended dose may cause serious health problems. In case of overdose, get medical help or contact a Poison Control Center right away. Quick medical attention is critical for adults as well as for children even if you do not noticve any signs or symptoms.

Directions

- do not take more than directed
- do not take more than 4 doses in any 24 hours
- this adult strength product is not intended for use in children under 12 year of age
- measure only with dosing cup provided
- keep dosing cup with product
- mL = mililiter
- TBSP = tablespoon
- dose as follows

Adults and children 12 years of age and over | 30 mL (2 tablespoons) every 6 hours
Children under 12 years of age | Do not use

when using day time and night time products, carefully read each label to ensure correct dosing

Other information

- Each 30 mL contains sodium 18 mg
- store between 15-30oC (59-86oF)
- do not refrigerate

Inactive ingredients

Citric acid, FD&C Yellow # 6, flavor, glycerin, honey, propylene glycol, purified water, sodium benzoate, sorbitol solution, sucralose

Questions or comments?

1-877-994-3666 Monday to Friday from 8 am to 6 pm, Central Time.

Distributed by:
Genomma Lab USA Inc.,
Houston, TX 77098

PRINCIPAL DISPLAY PANEL - 118 ml Kit Carton

Tukol®

HONEY

Day Time
Multi symptom

VALUE PACK
COLD & FLU

Acetaminophen/ Dextromethorphan HBr /
Phenylephrine HCl

Ages
12+

NATURAL

HONEY
FLAVOR

Relieves:

- HEADACHE, SORE THROAT, FEVER
- MINOR ACHES AND PAINS
- NASAL CONGESTION AND COUGH

4 FL OZ (118 ml)

Night Time
Multi symptom

Acetaminophen/ Dextromethorphan HBr /
Doxylamine succinate

Ages
12+

NATURAL

HONEY
FLAVOR

Relieves:

- HEADACHE, SORE THROAT, FEVER
- MINOR ACHES AND PAINS
- SNEEZING, RUNNY NOSE
- COUGH

4 FL OZ (118 ml)